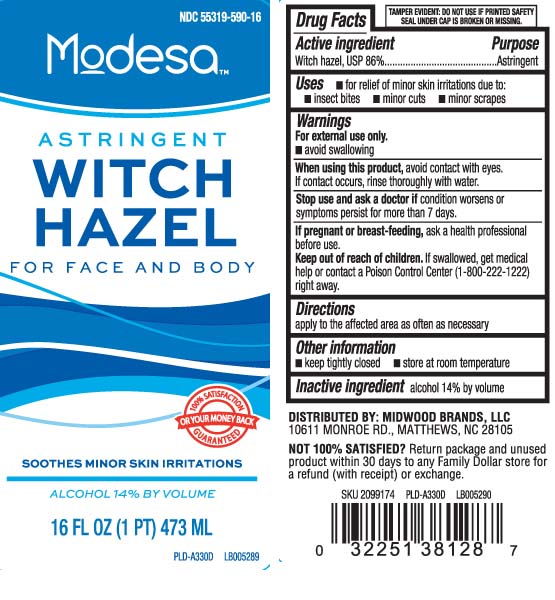 DRUG LABEL: Witch Hazel
NDC: 55319-590 | Form: LIQUID
Manufacturer: Family Dollar (FAMILY WELLNESS)
Category: otc | Type: HUMAN OTC DRUG LABEL
Date: 20250206

ACTIVE INGREDIENTS: WITCH HAZEL 842 mg/1 mL
INACTIVE INGREDIENTS: ALCOHOL

Drug Facts

Active ingredient

Witch hazel 86%

Purpose

Astringent

Uses

- for relief of minor skin irritations due to:
  - insect bites
  - minor cuts
  - minor scrapes

Warnings

- for external use only
- avoid swallowing

When using this product

avoid contact with eyes. If contact occurs, rinse thoroughly with water.

Stop use and ask a doctor if

condition worsens or symptoms persist for more than 7 days.

If pregnant or breast-feeding,

ask a health professional before use.

Keep out of reach of children.

If swallowed, get medical help or contact a Poison Control Center (1-800-222-1222) right away.

Directions

apply to the affected area as often as necessary.

Other information

- keep tightly closed
- store at room temperature

Inactive ingredient

alcohol 14% by volume

Principal Display Panel

Modesa

ASTRINGENT

WITCH HAZEL

For Face and Body

SOOTHES MINOR SKIN IRRITATIONS

ALCOHOL 14% BY VOLUME

FL OZ (mL)

TAMPER EVIDENT: DO NOT USE IF PRINTED SAFETY SEAL UNDER CAP IS BROKEN OR MISSING.

DISTRIBUTED BY: MIDWOOD BRANDS, LLC

10611 MONROE RD, MATTHEWS, NC 28105

Package Label

MODESA-FAMILY WELLNESS Witch Hazel